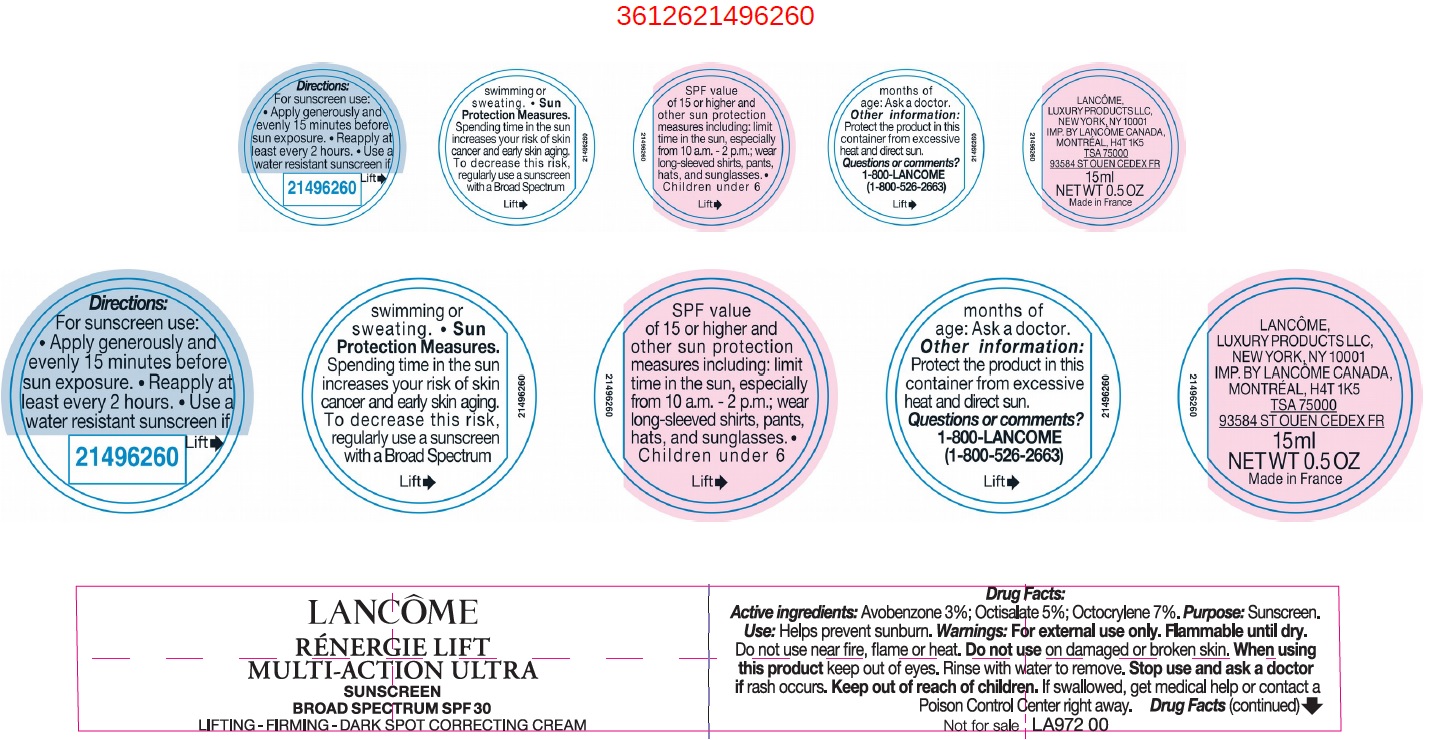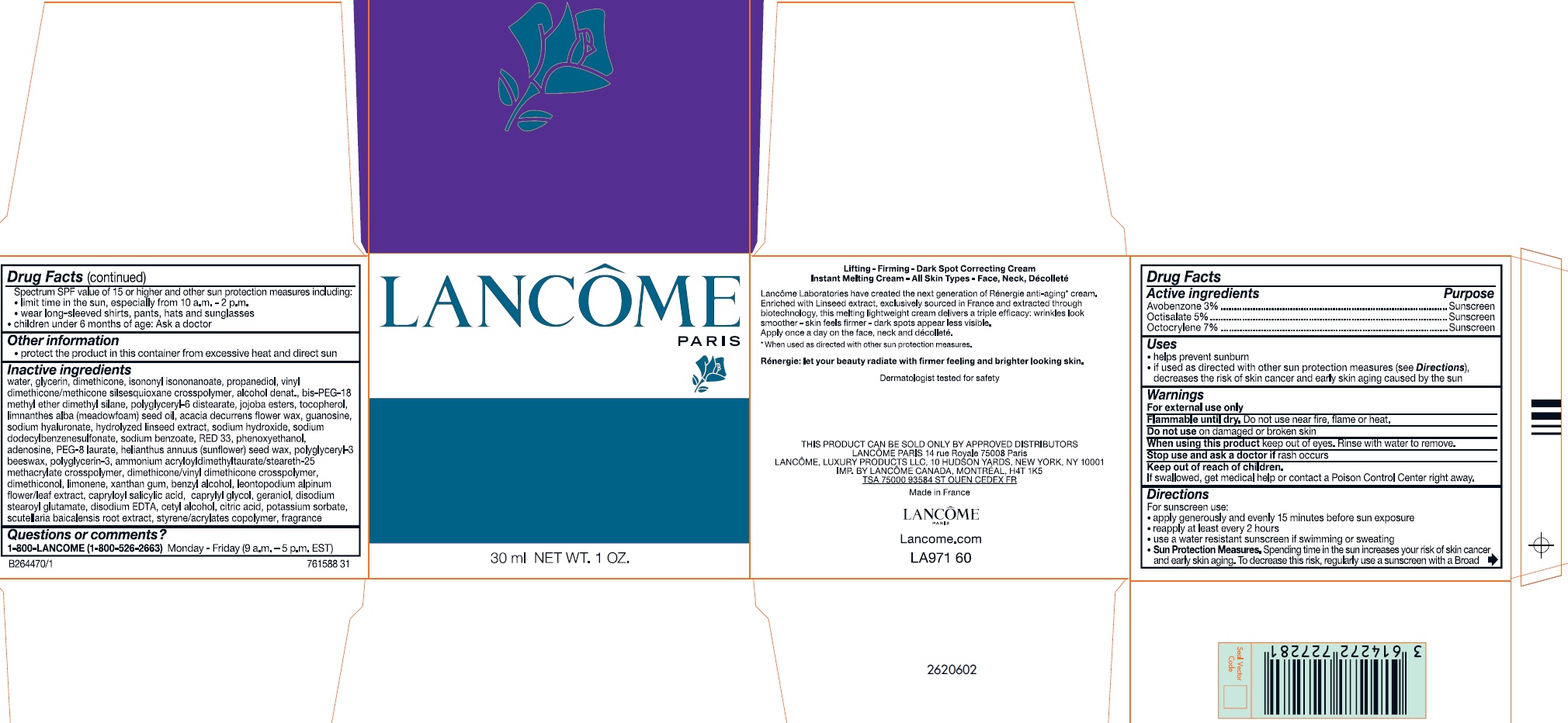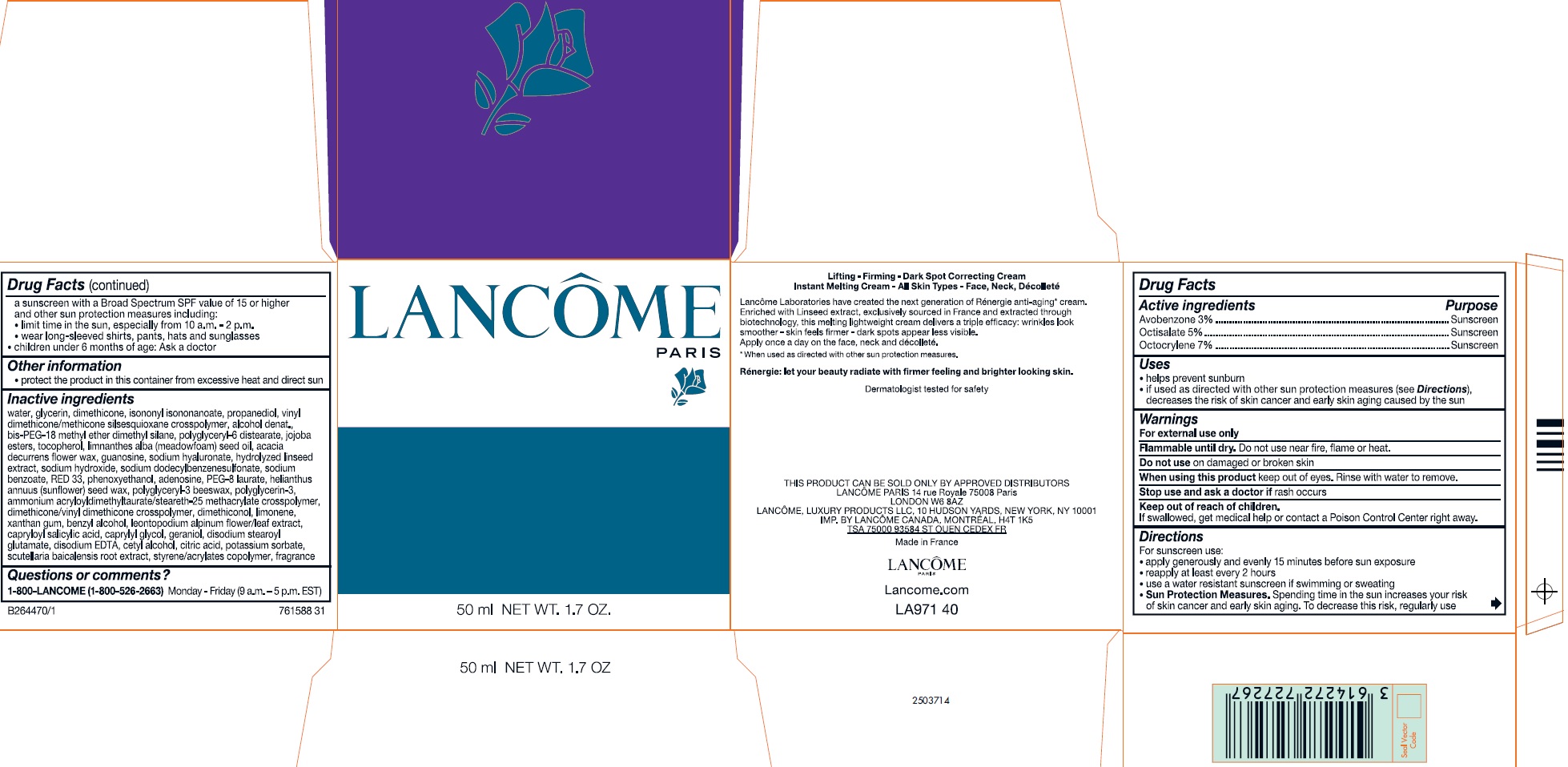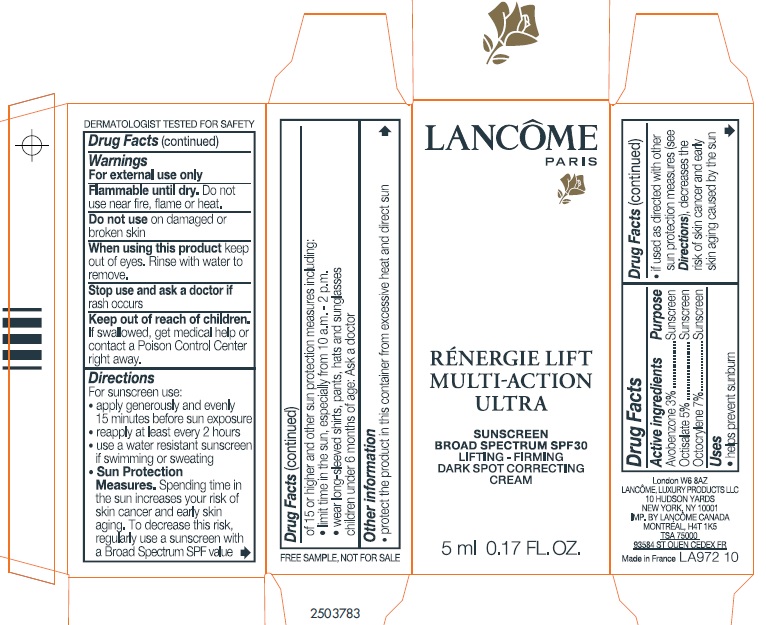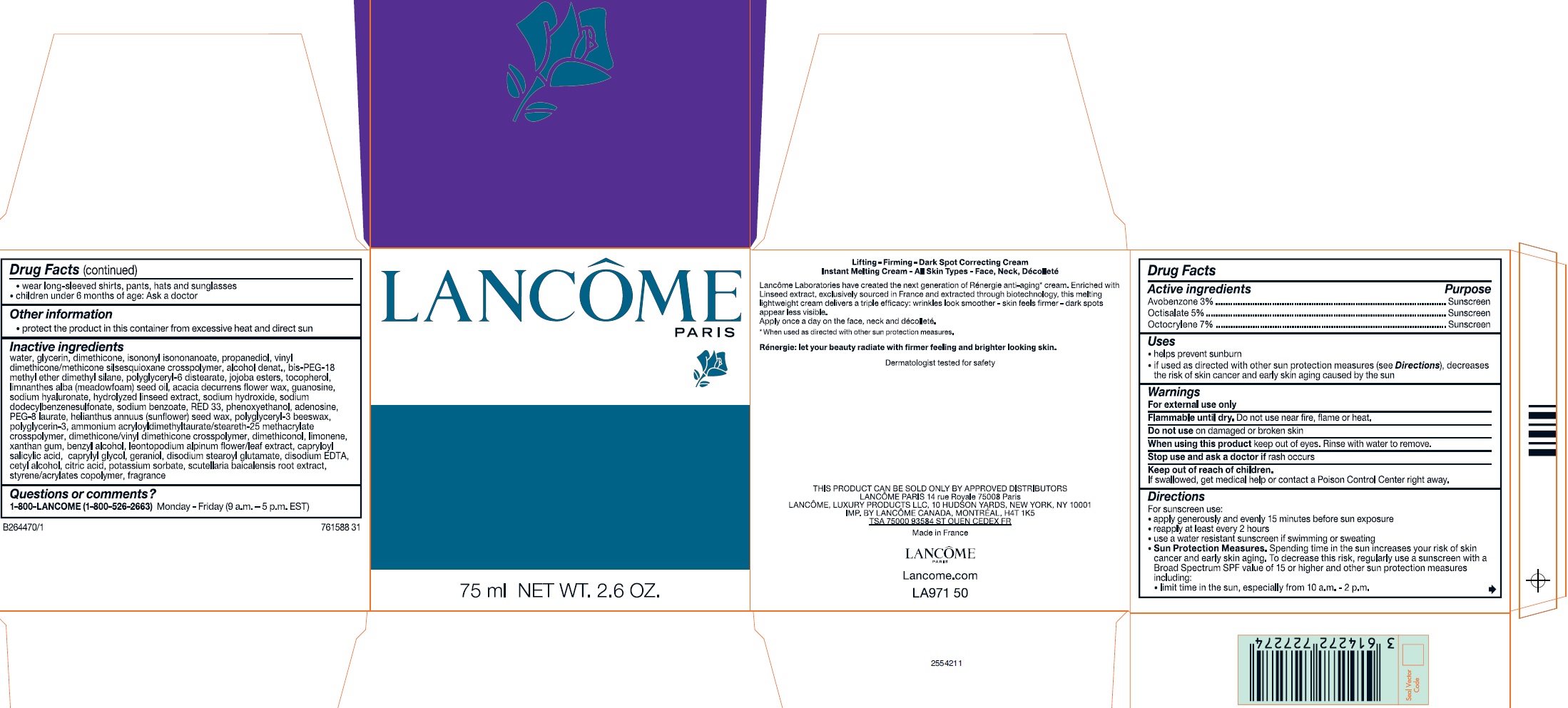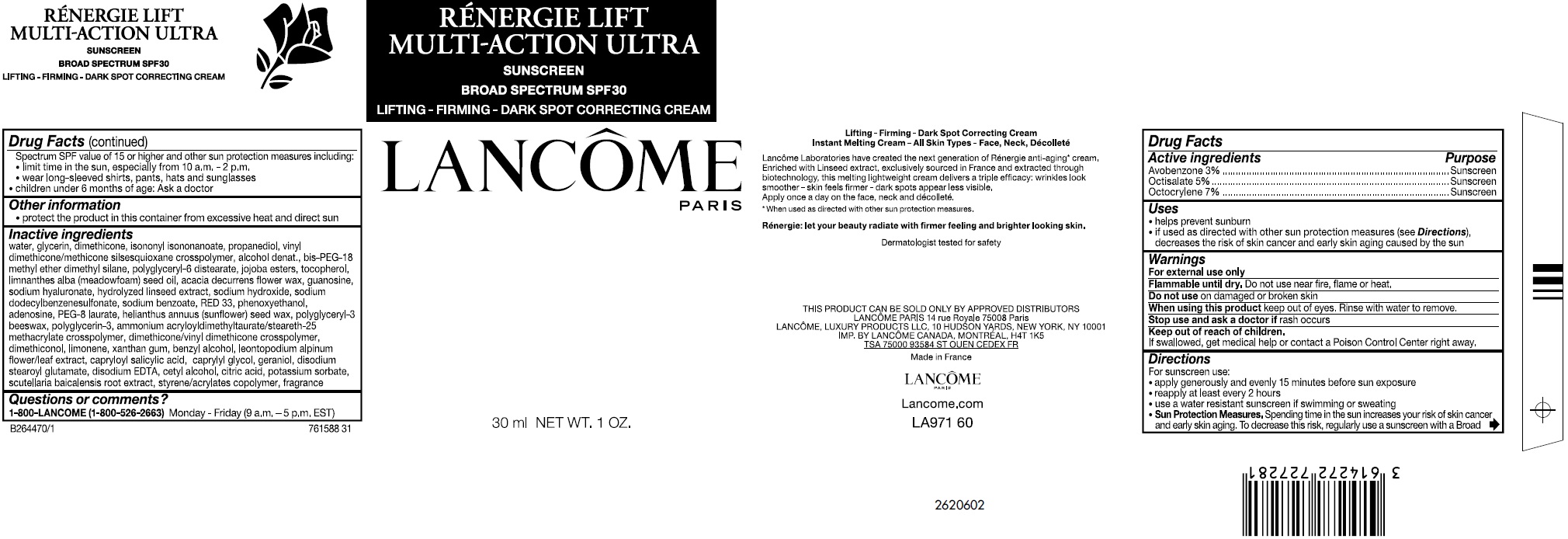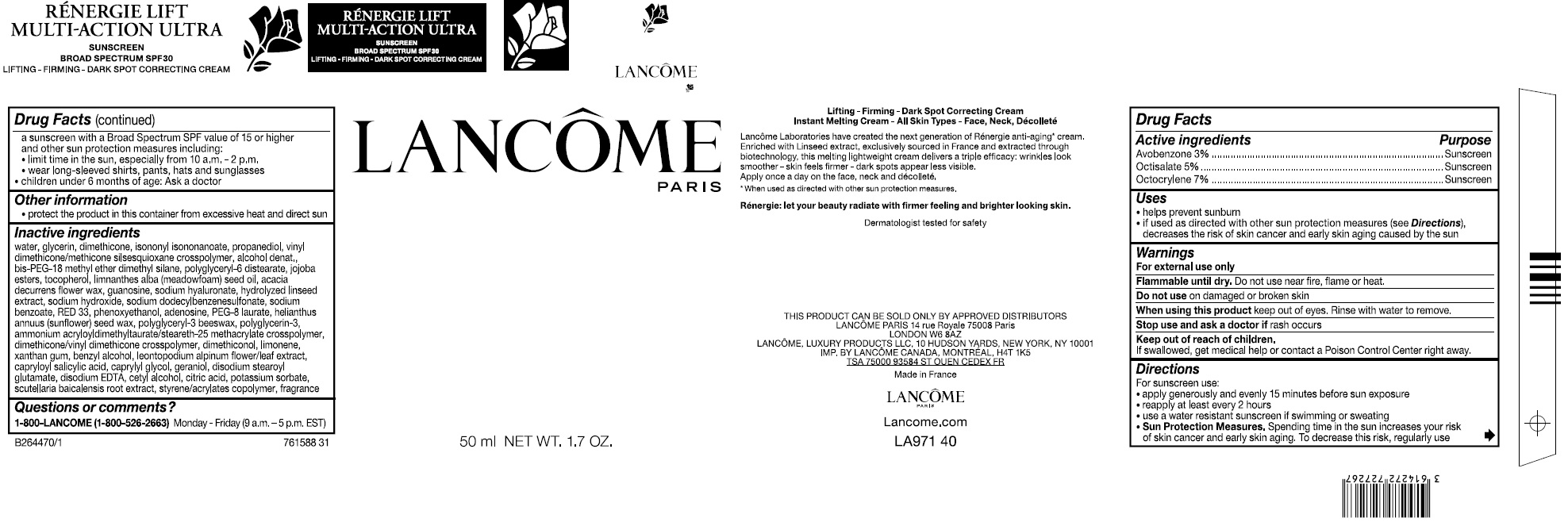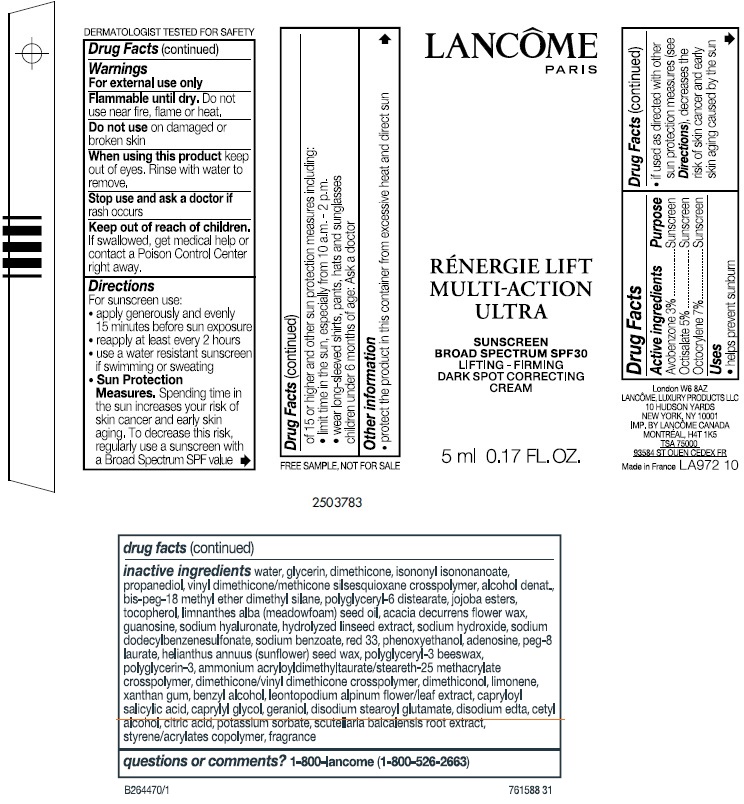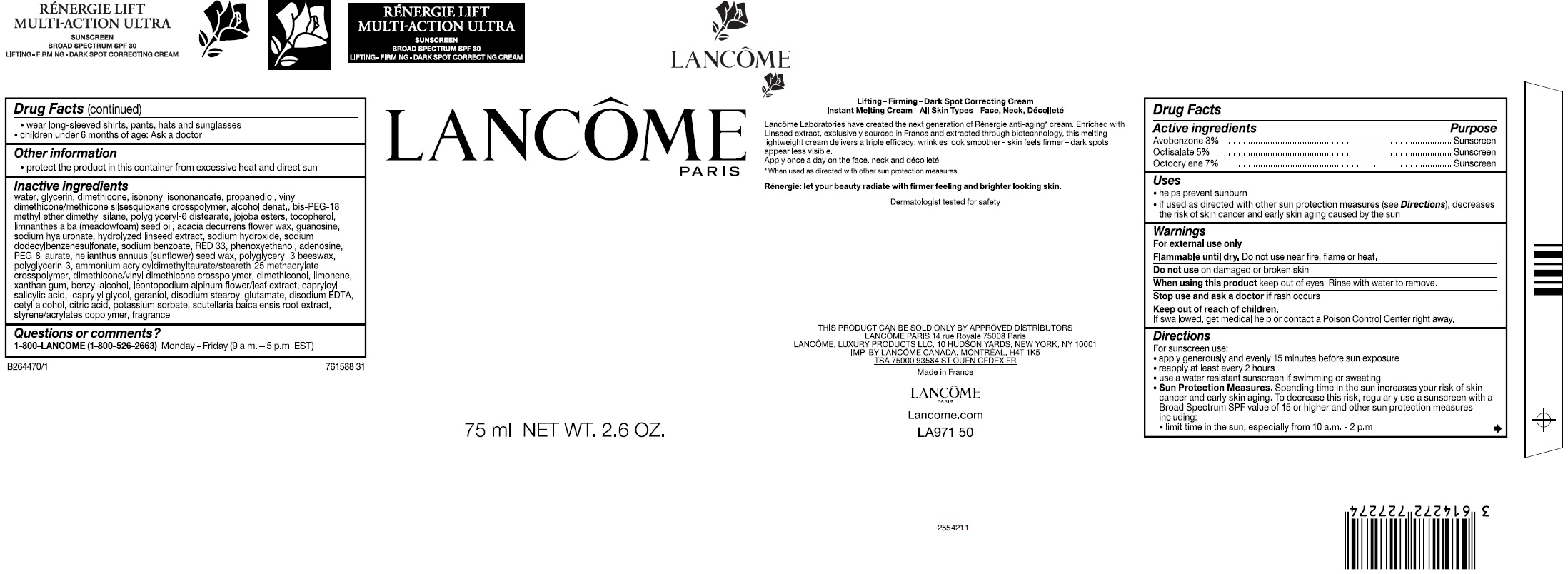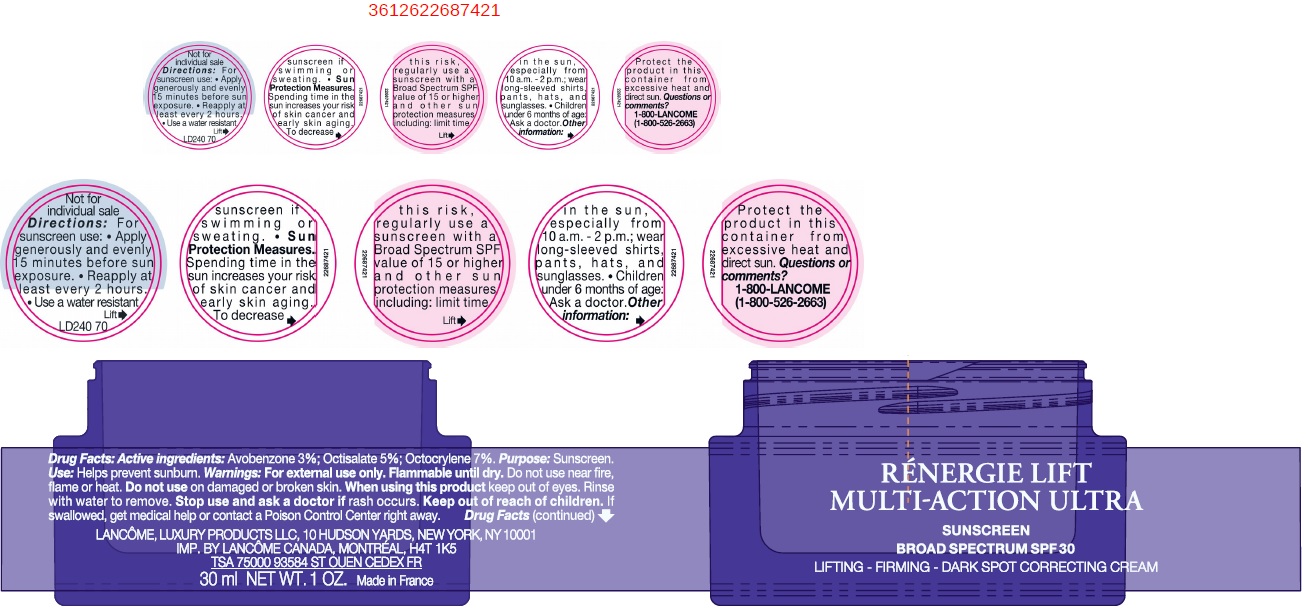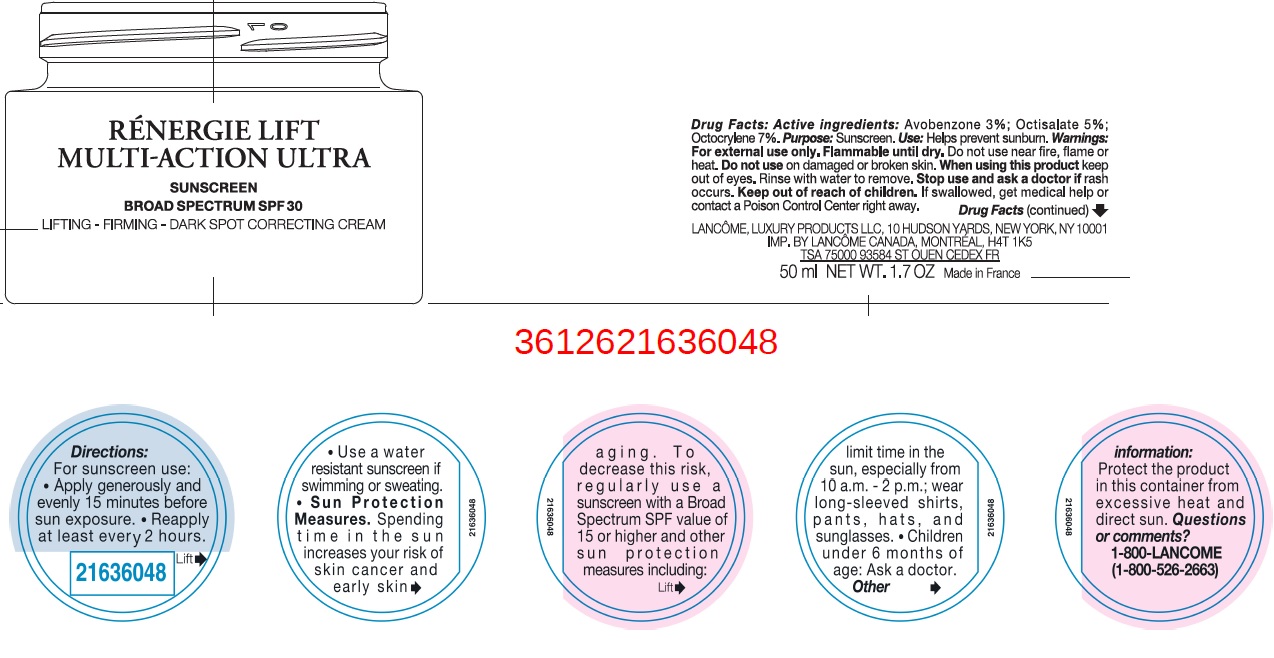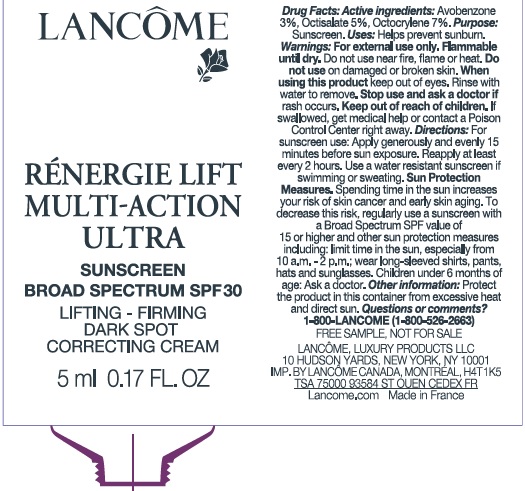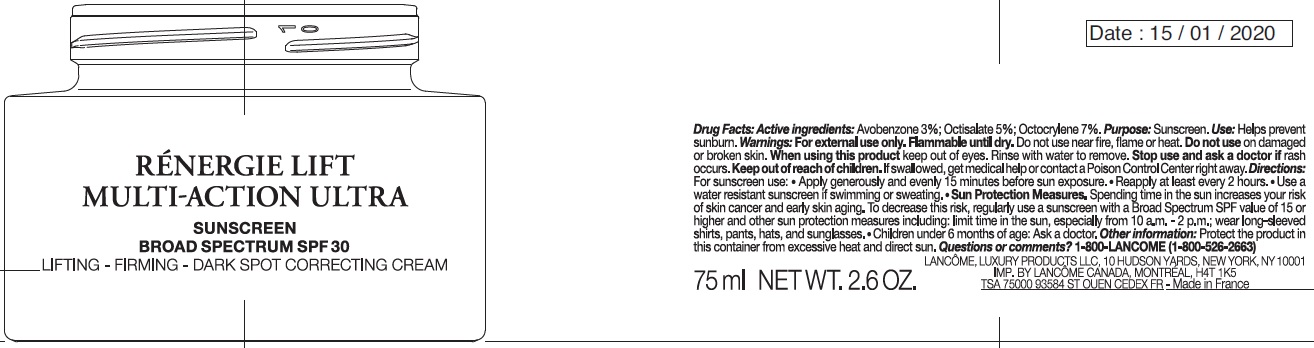 DRUG LABEL: Rener lift multi action ultra SPF 30
NDC: 70581-020 | Form: CREAM
Manufacturer: BPS 60
Category: otc | Type: HUMAN OTC DRUG LABEL
Date: 20240118

ACTIVE INGREDIENTS: AVOBENZONE 30 mg/1 mL; OCTISALATE 50 mg/1 mL; OCTOCRYLENE 70 mg/1 mL
INACTIVE INGREDIENTS: WATER; GLYCERIN; DIMETHICONE; ISONONYL ISONONANOATE; PROPANEDIOL; VINYL DIMETHICONE/METHICONE SILSESQUIOXANE CROSSPOLYMER; ALCOHOL; BIS-PEG-18 METHYL ETHER DIMETHYL SILANE; POLYGLYCERYL-6 DISTEARATE; TOCOPHEROL; MEADOWFOAM SEED OIL; ACACIA DECURRENS FLOWER WAX; GUANOSINE; HYALURONATE SODIUM; SODIUM HYDROXIDE; SODIUM DODECYLBENZENESULFONATE; SODIUM BENZOATE; D&C RED NO. 33; PHENOXYETHANOL; ADENOSINE; PEG-8 LAURATE; HELIANTHUS ANNUUS SEED WAX; POLYGLYCERIN-3; AMMONIUM ACRYLOYLDIMETHYLTAURATE; LIMONENE, (+)-; XANTHAN GUM; BENZYL ALCOHOL; LEONTOPODIUM NIVALE SUBSP. ALPINUM FLOWERING TOP; CAPRYLOYL SALICYLIC ACID; CAPRYLYL GLYCOL; GERANIOL; DISODIUM STEAROYL GLUTAMATE; EDETATE DISODIUM ANHYDROUS; CETYL ALCOHOL; CITRIC ACID MONOHYDRATE; POTASSIUM SORBATE; SCUTELLARIA BAICALENSIS ROOT

Rener lift multi action ultra SPF 30

Active ingredients:

Avobenzone 3%

Octisalate 5%

Octocrylene 7%

Purpose:

Sunscreen.

Uses

- helps prevent sunburn
- if used as directed with other sun protection measures (see), decreases the risk of skin cancer and early skin aging caused by the sun Directions

Warnings:

For external use only.

Do not use near fire, flame or heat. Flammable until dry.

Do not use

on damaged or broekn skin

When using this product

keep out of eyes. Rinse with water to remove.

Stop use and and ask a doctor

if rash occurs.

Keep out of reach of children.

If swallowed, get medical help or contact a Poison Control Center right away.

Directions:

For sunscreen use:

- apply generously and evenly 15 minutes before sun exposure
- reapply at least every 2 hours
- use a water resistant sunscreen if swimming or sweating
- Spending time in the sun increases your risk of skin cancer and early sking aging. To decrease this risk, regularly use a sunscreen with a Broad Spectrum SPF value of 15 or higher and other sun protection measures including: Sun Protection Measures.
- limit time in the sun, especially from 10 a.m. - 2 p.m.
- wear long-sleeved shirts, pants, hats, and sunglasses.
- Children under 6 months of age: Ask a doctor.

Other information:

- protect the product in this container from excessive heat and direct sun

Inactive ingredients

water, glycerin, dimethicone, isononyl isononanoate, propanediol, vinyl dimethicone/methicone silsesquioxane crosspolymer, alcohol denat., bis-PEG-18 methyl ether dimethyl silane, polyglyceryl-6 distearate, jojoba esters, tocopherol, limnanthes alba (meadowfoam) seed oil, acacia decurrens flower wax, guanosine, sodium hyaluronate, hydrolyzed linseed extract, sodium hydroxide, sodium dodecylbenzenesulfonate, sodium benzoate, RED 33, phenoxyethanol, adenosine, PEG-8 laurate, helianthus annuus (sunflower) seed wax, polyglyceryl-3 beeswax, polyglycerin-3, ammonium acryloyldimethyltaurate/steareth-25 methacrylate crosspolymer, dimethicone/vinyl dimethicone crosspolymer, dimethiconol, limonene, xanthan gum, benzyl alcohol, leontopodium alpinum flower/leaf extract, capryloyl salicylic acid, caprylyl glycol, geraniol, disodium stearoyl glutamate, disodium EDTA, cetyl alcohol, citric acid, potassium sorbate, scutellaria baicalensis root extract, styrene/acrylates copolymer, fragrance

Questions or comments?

Monday - Friday (9 a.m. - 5 p.m. EST) 1-800-LANCOME (1-800-526-2663)